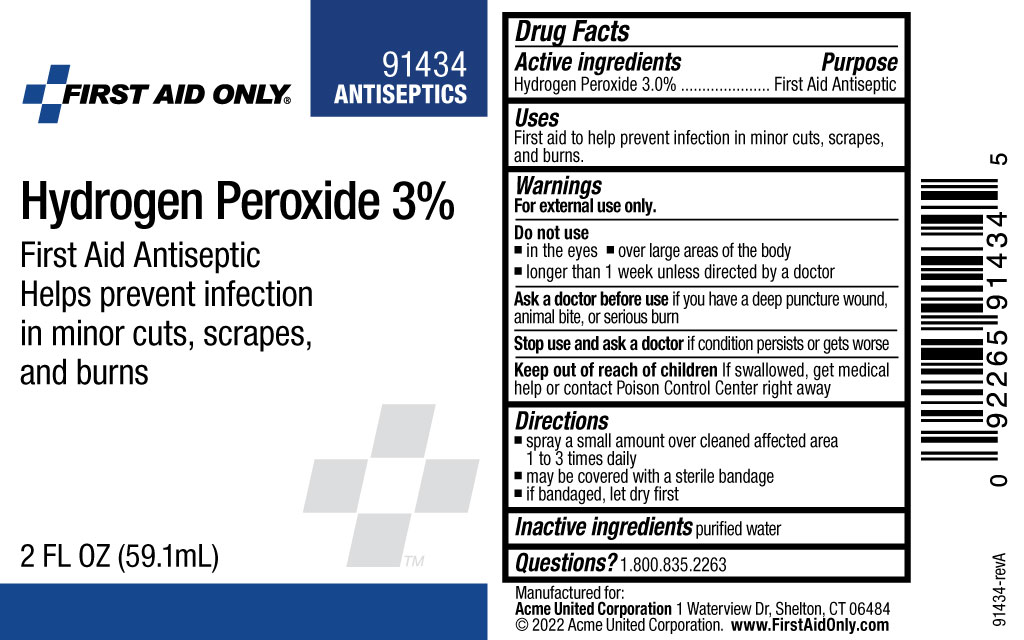 DRUG LABEL: First Aid Only Hydrogen Peroxide 3%
NDC: 0924-0935 | Form: SPRAY
Manufacturer: Acme United Corporationn
Category: otc | Type: HUMAN OTC DRUG LABEL
Date: 20241126

ACTIVE INGREDIENTS: HYDROGEN PEROXIDE 30 mg/1 mL
INACTIVE INGREDIENTS: WATER

First Aid Only Hydogen Peroxide 3% (Spray)

Drug Facts

Active Ingredients

Hydrogen Peroxide 3.0%

Purpose

First Aid Antiseptic

Uses

First aid to help prevent infection in minor cuts, scrapes and burns.

Warnings

For external use only.

Do not use

- in the eyes
- over large areas of the body
- longer than 1 week unless directed by a doctor

Ask a doctor before use if you have a deep puncture wound, animal bite, or serious burn

Stop use and ask a doctor if condition persists or gets worse

Keep out of reach of children. If swallowed, get medical help or contact Poison Control Center right away.

Directions

- spray a small amount over cleaned affected area 1 to 3 times daily
- may be covered with a sterile bandage
- if bandaged, let dry first

Inactive ingredients

purified water

Questions? 1.800.835.2263

Bottle Label